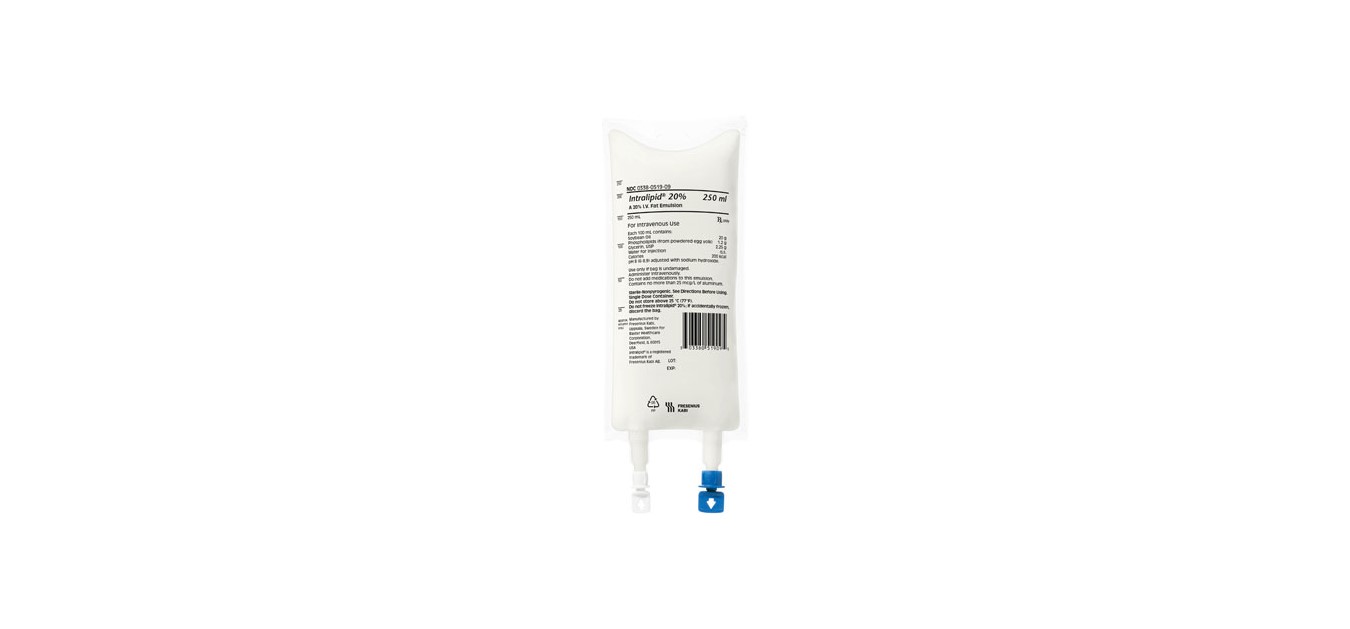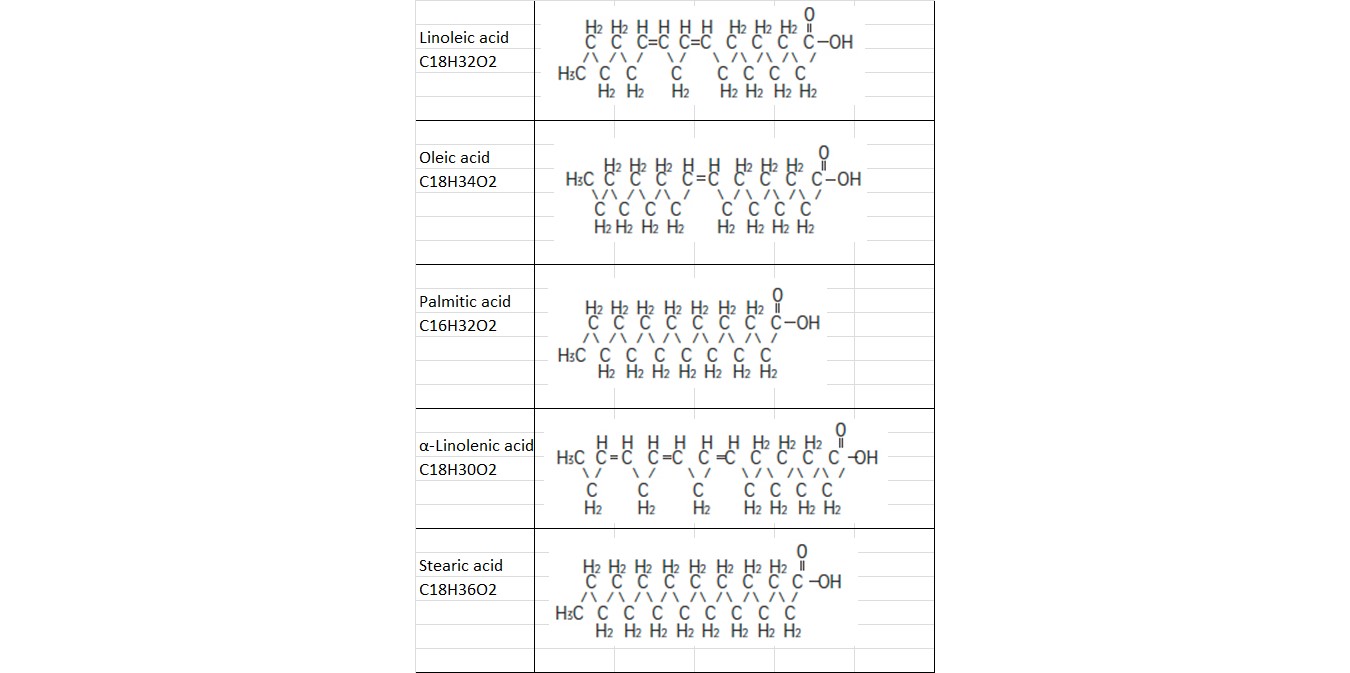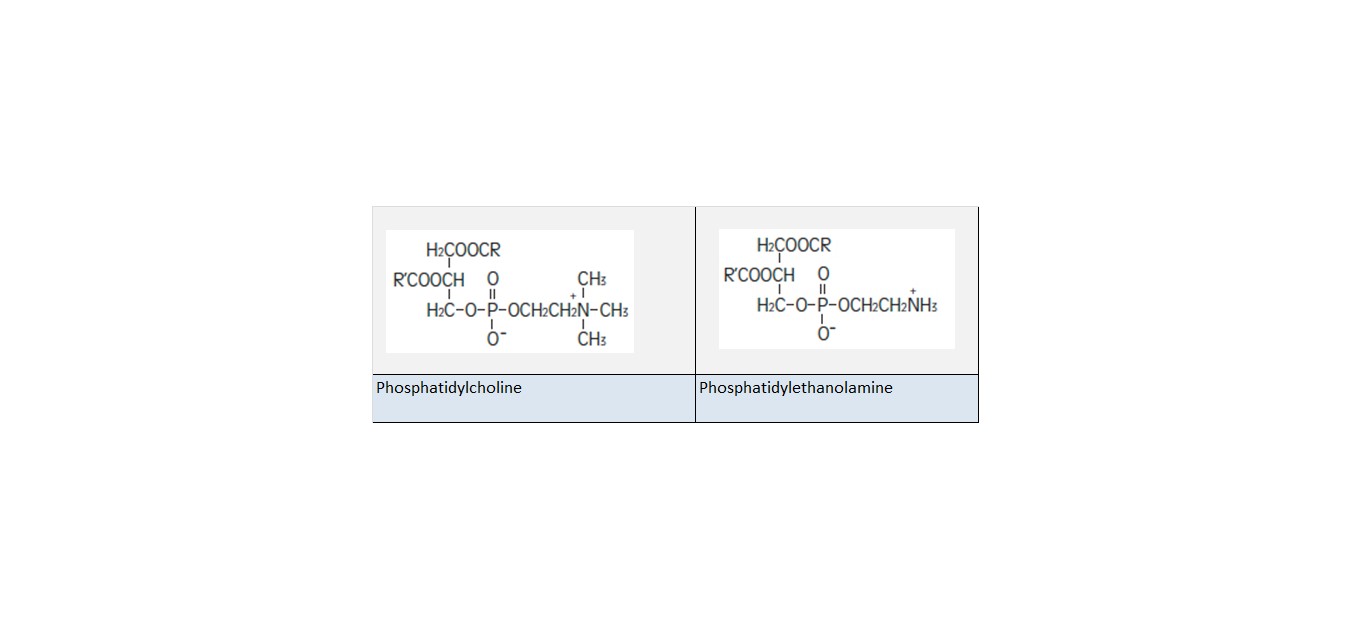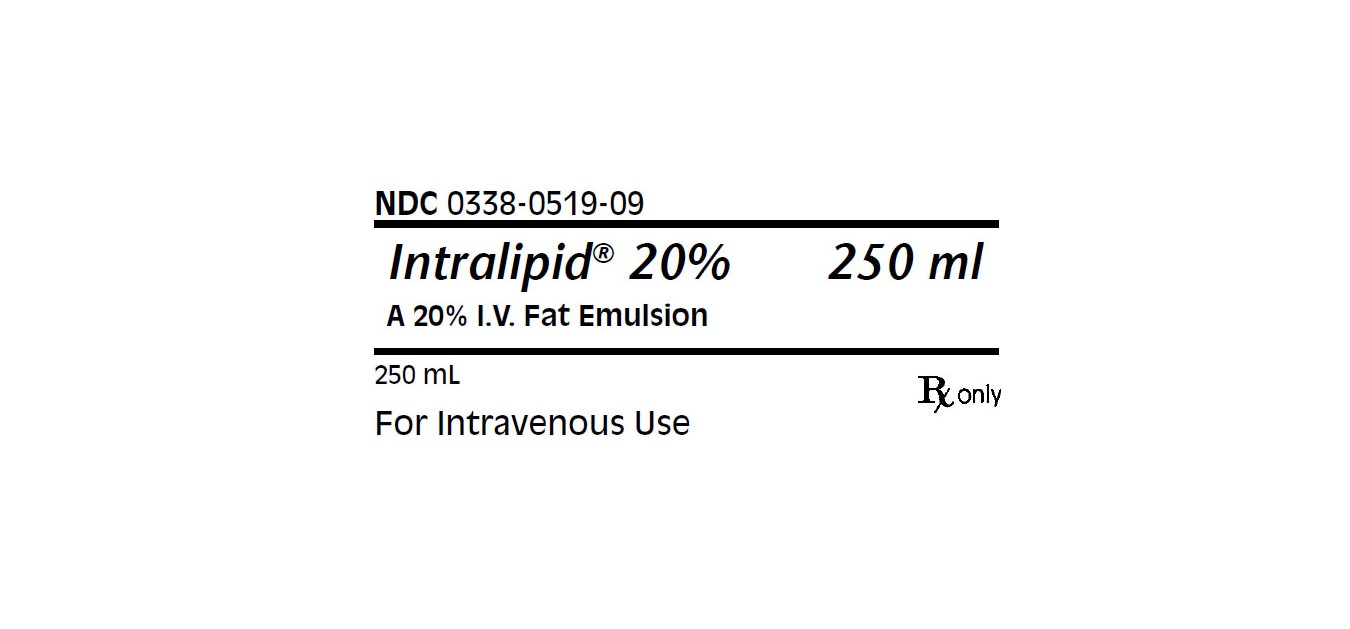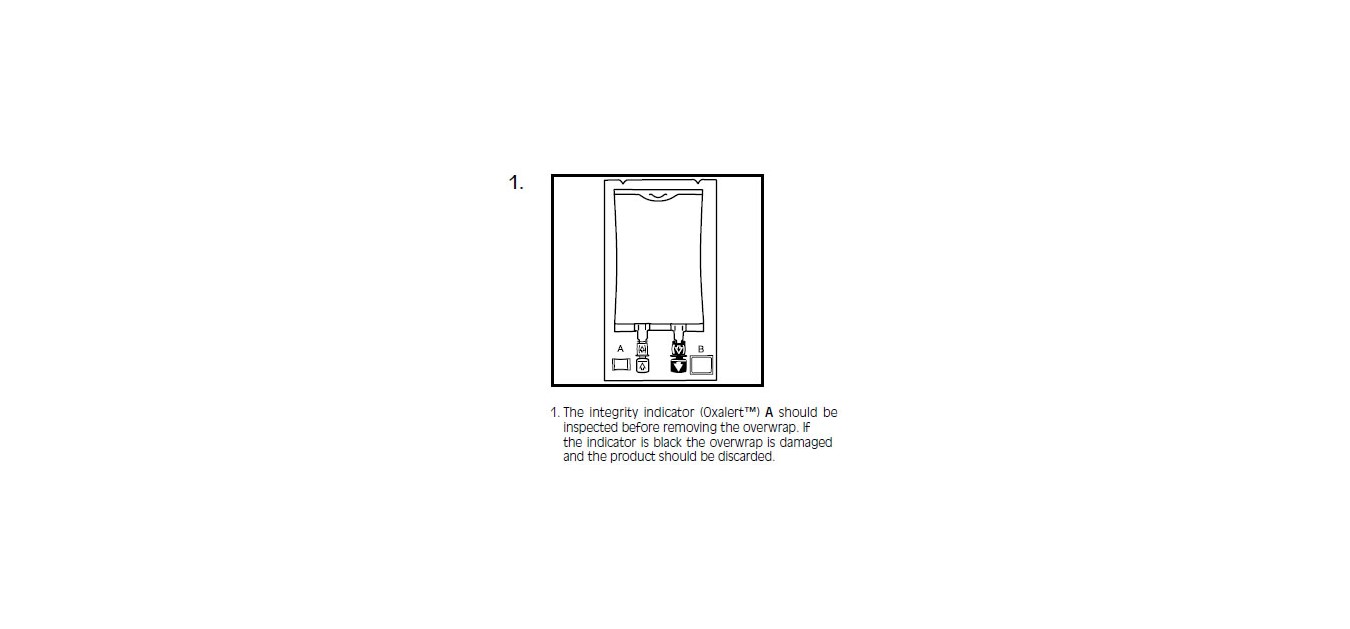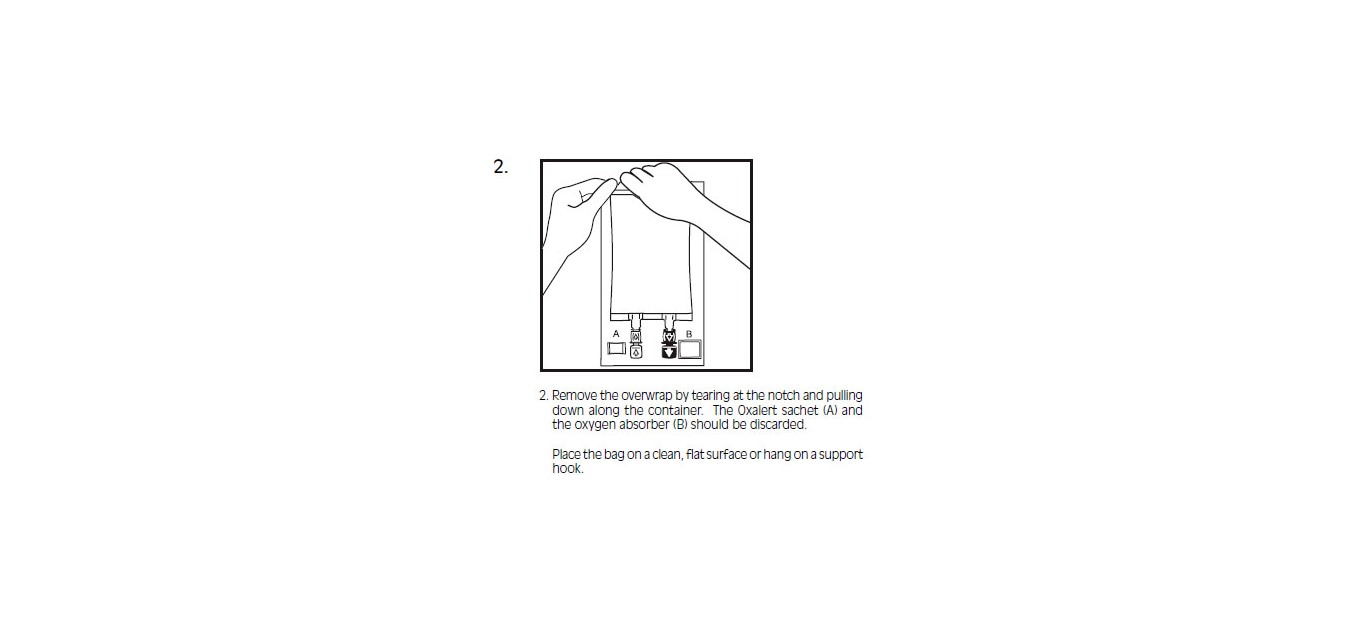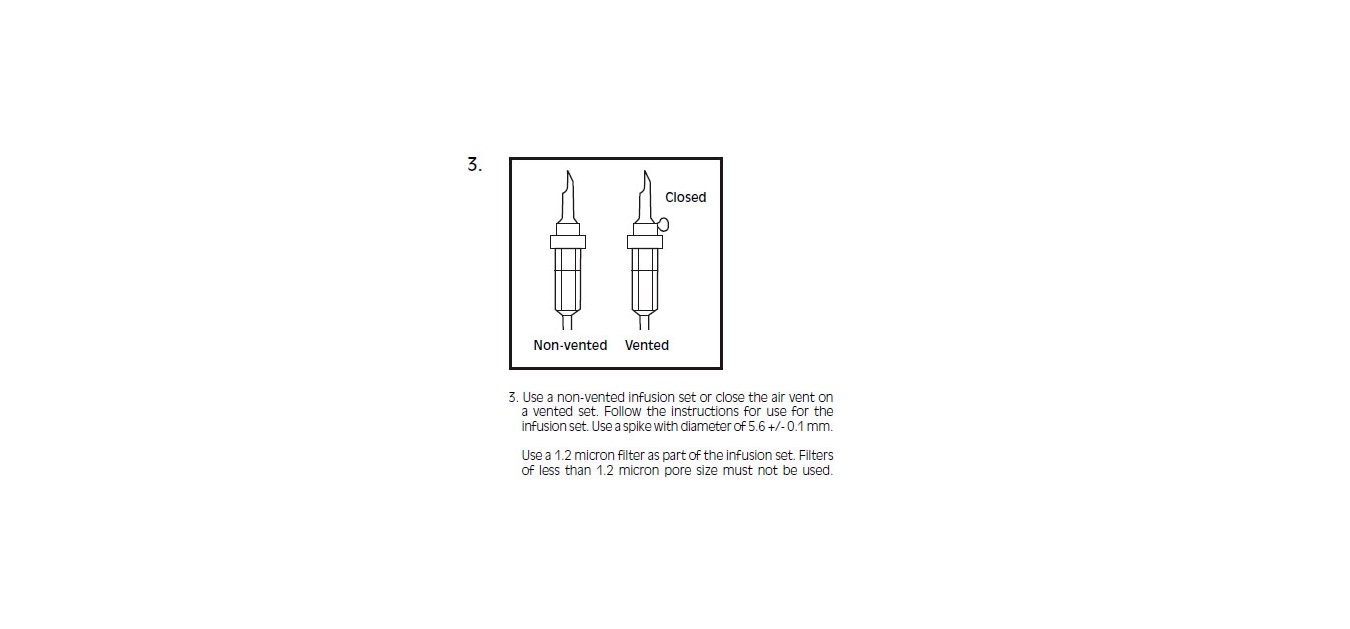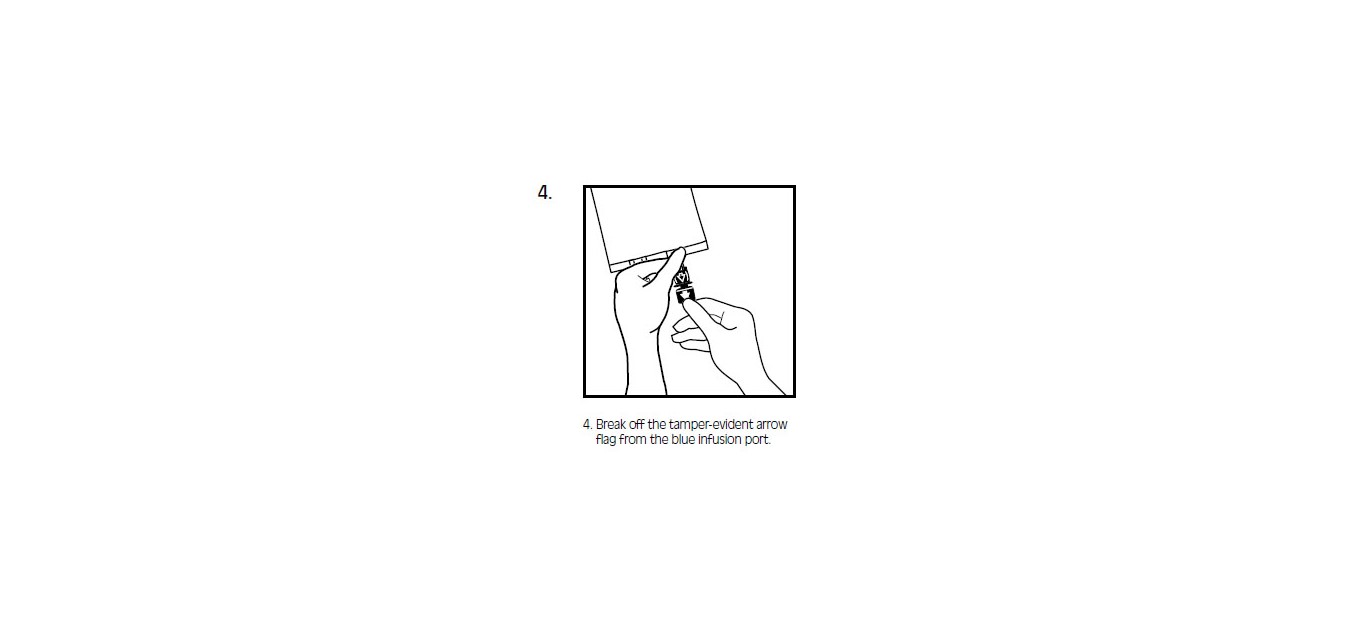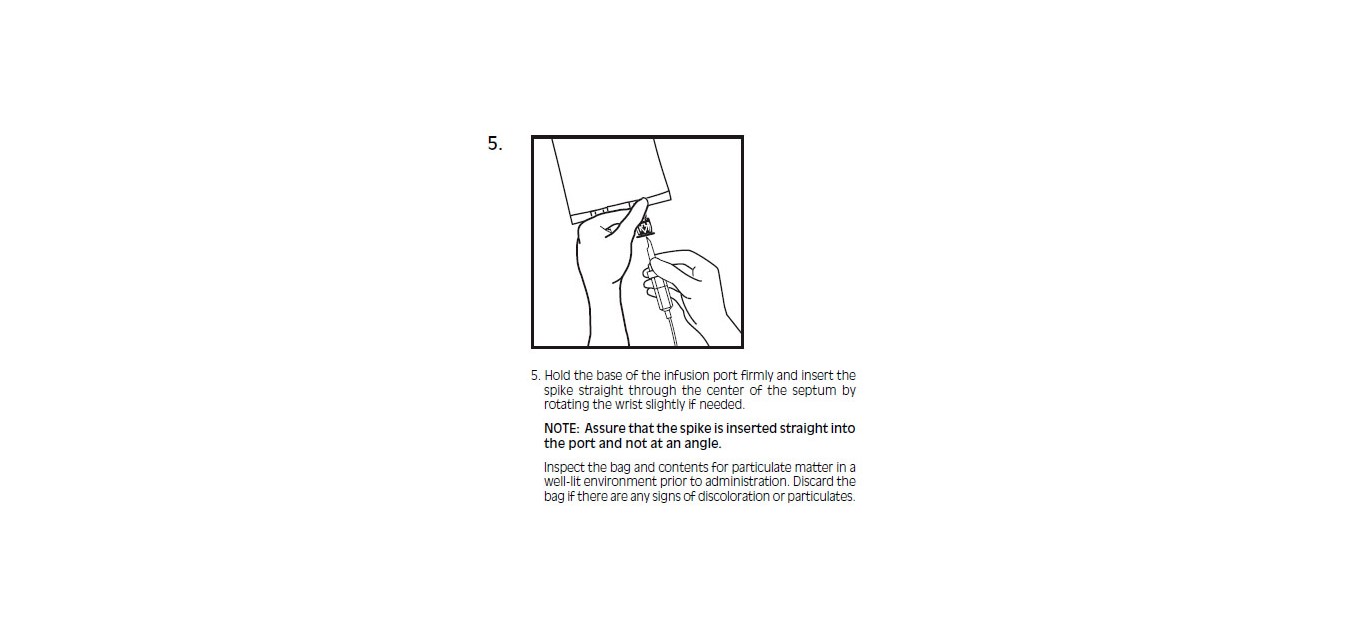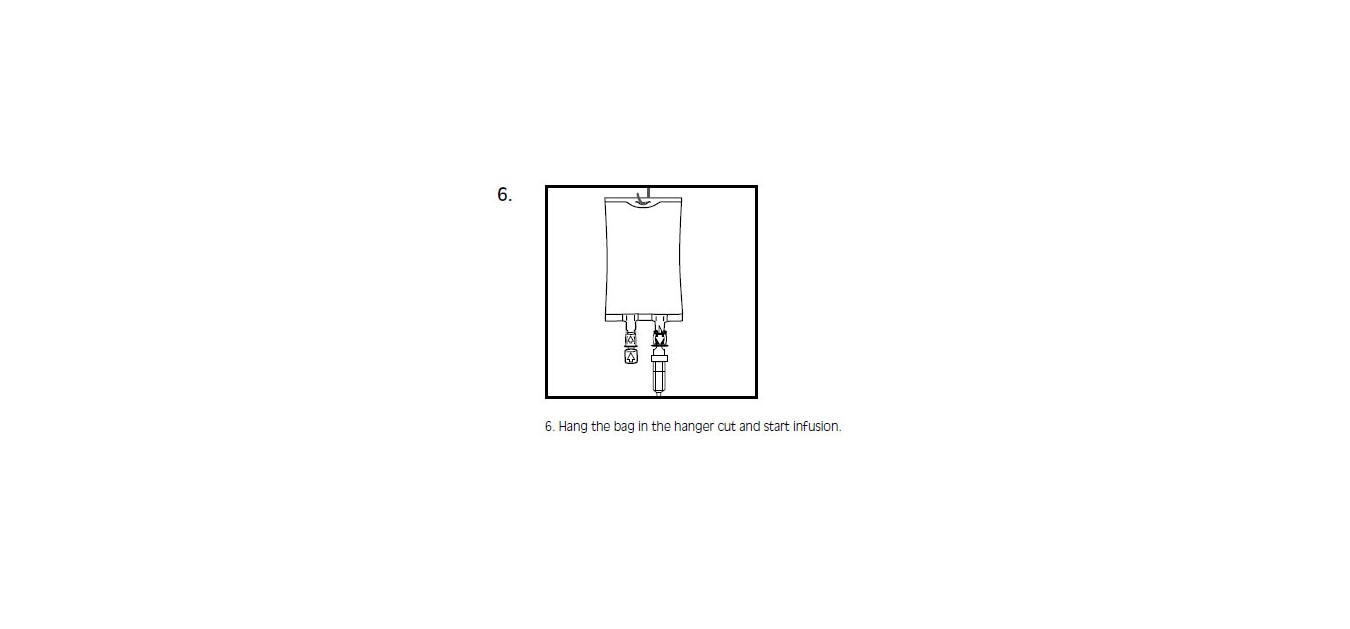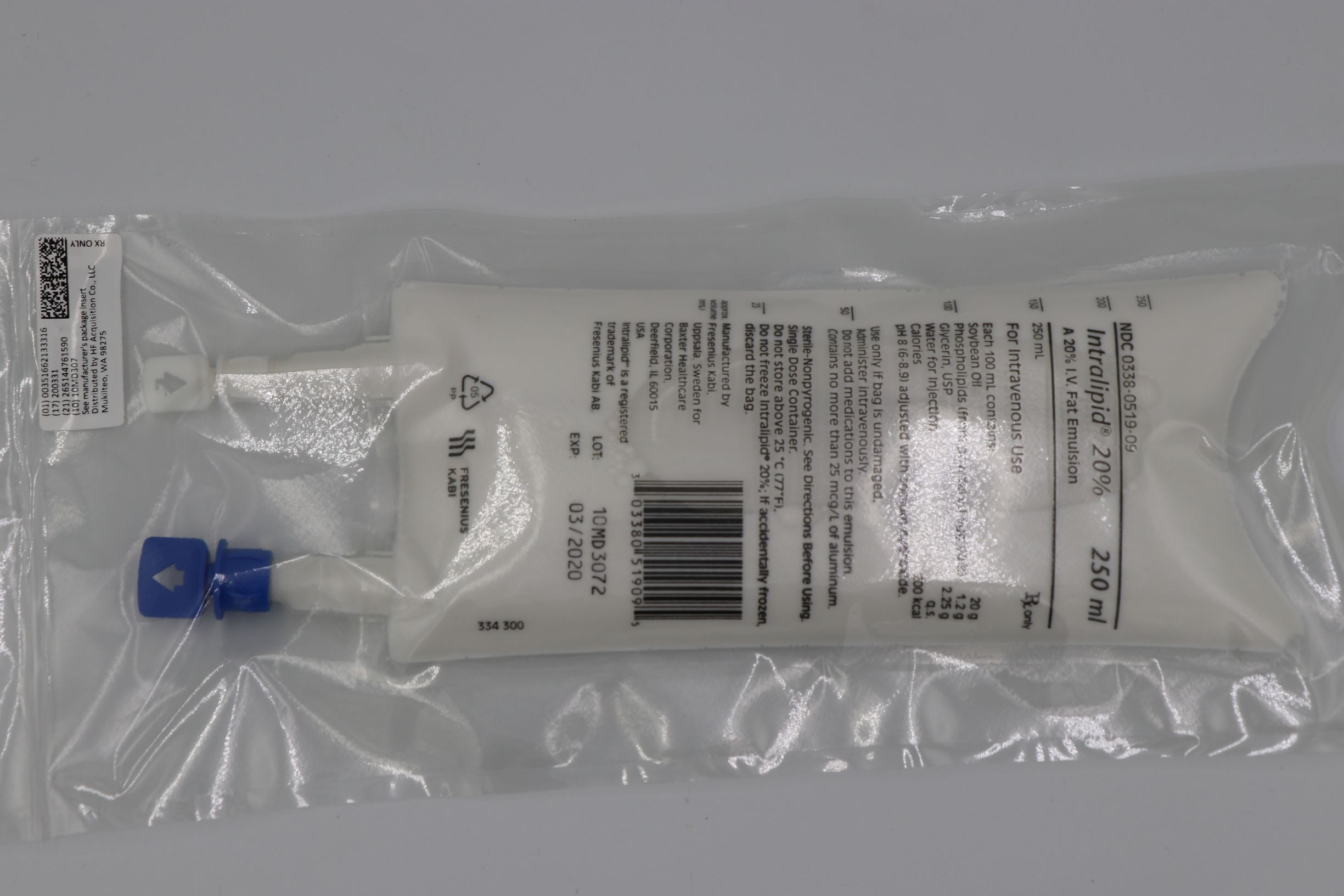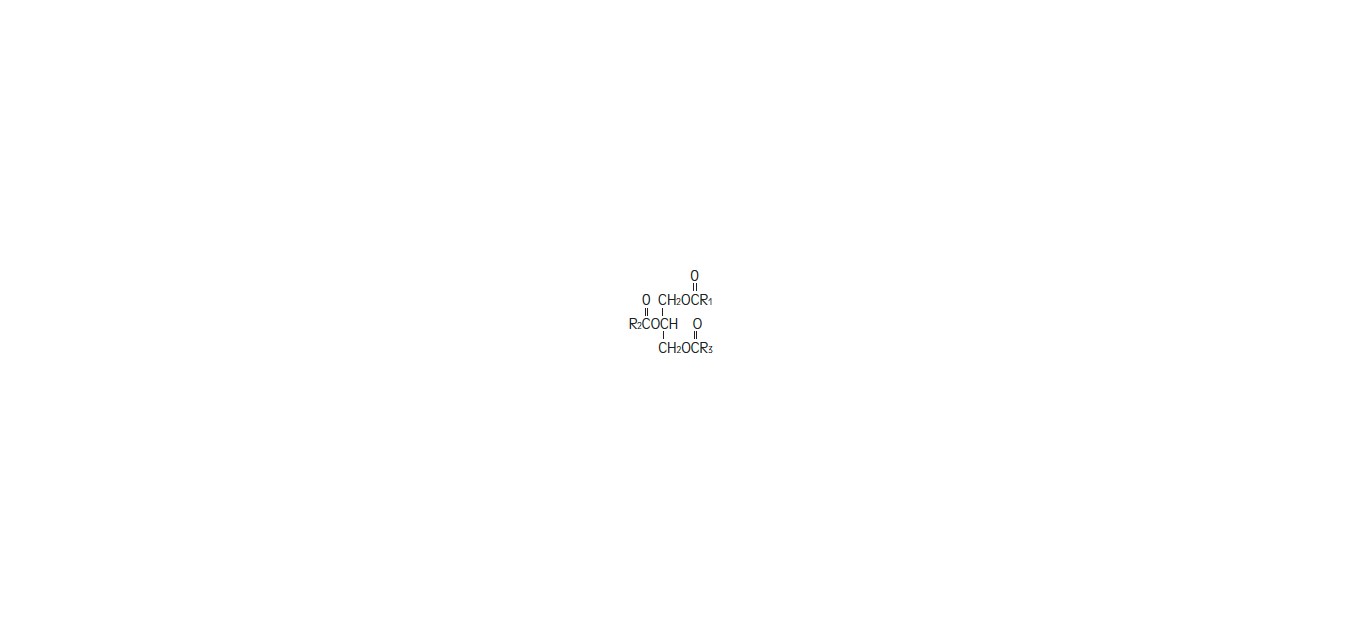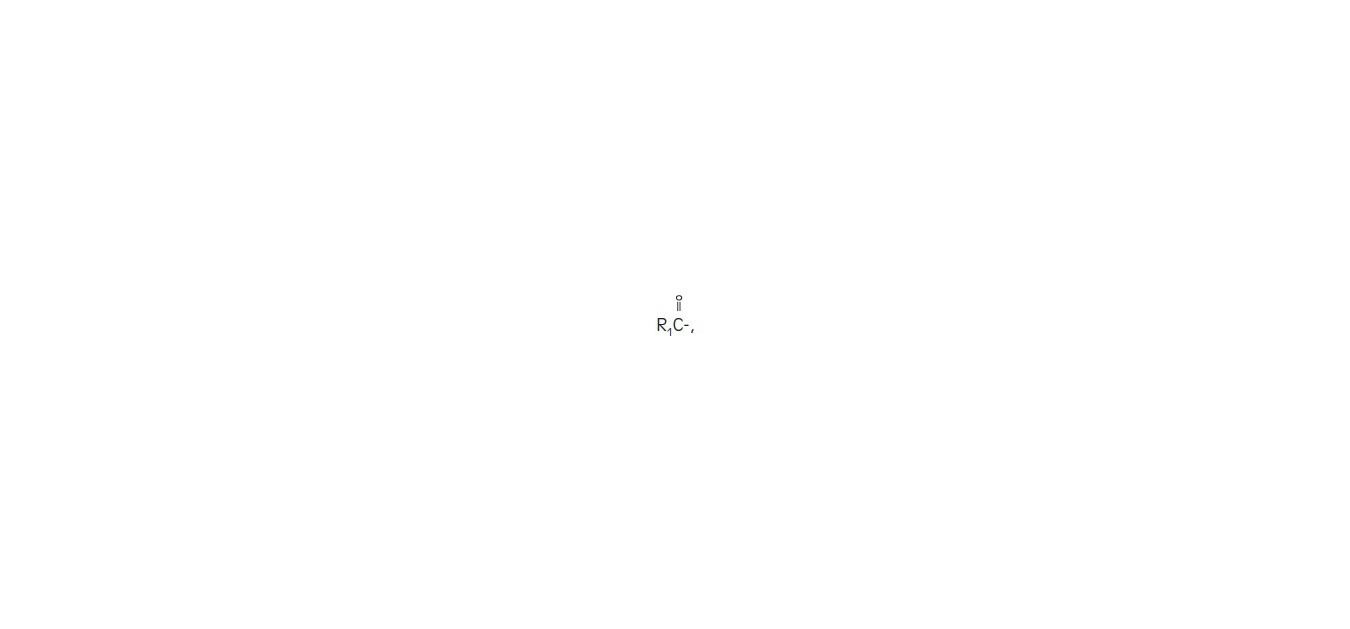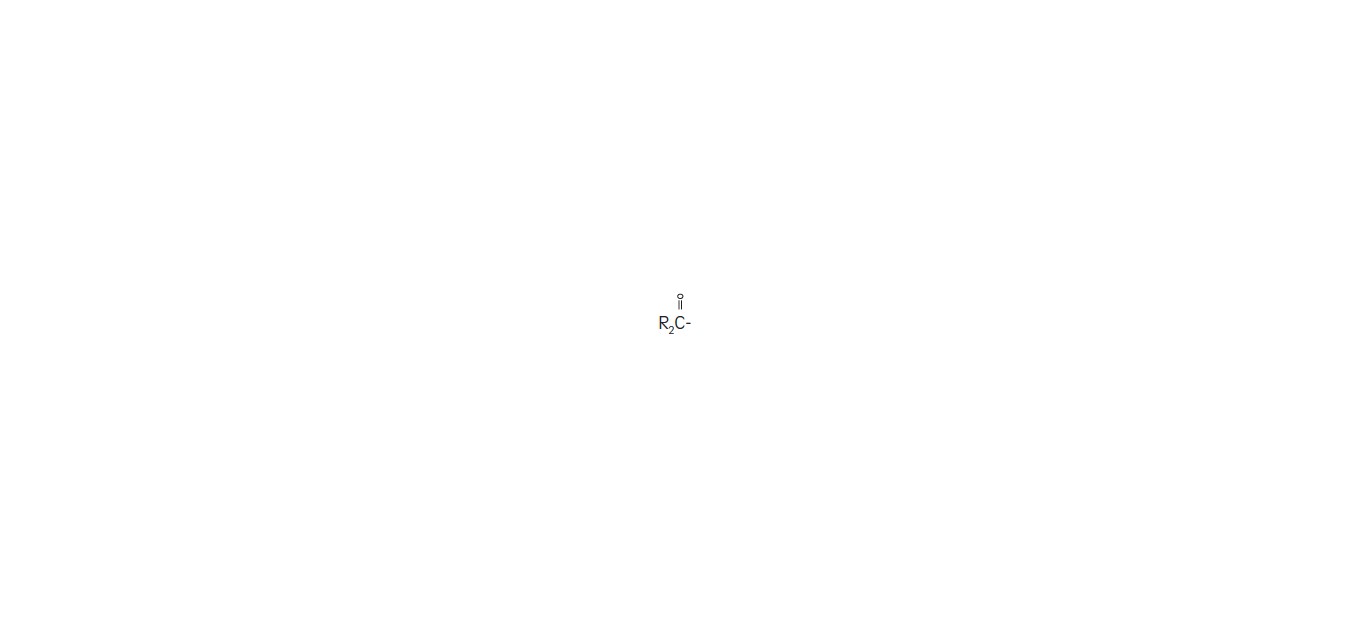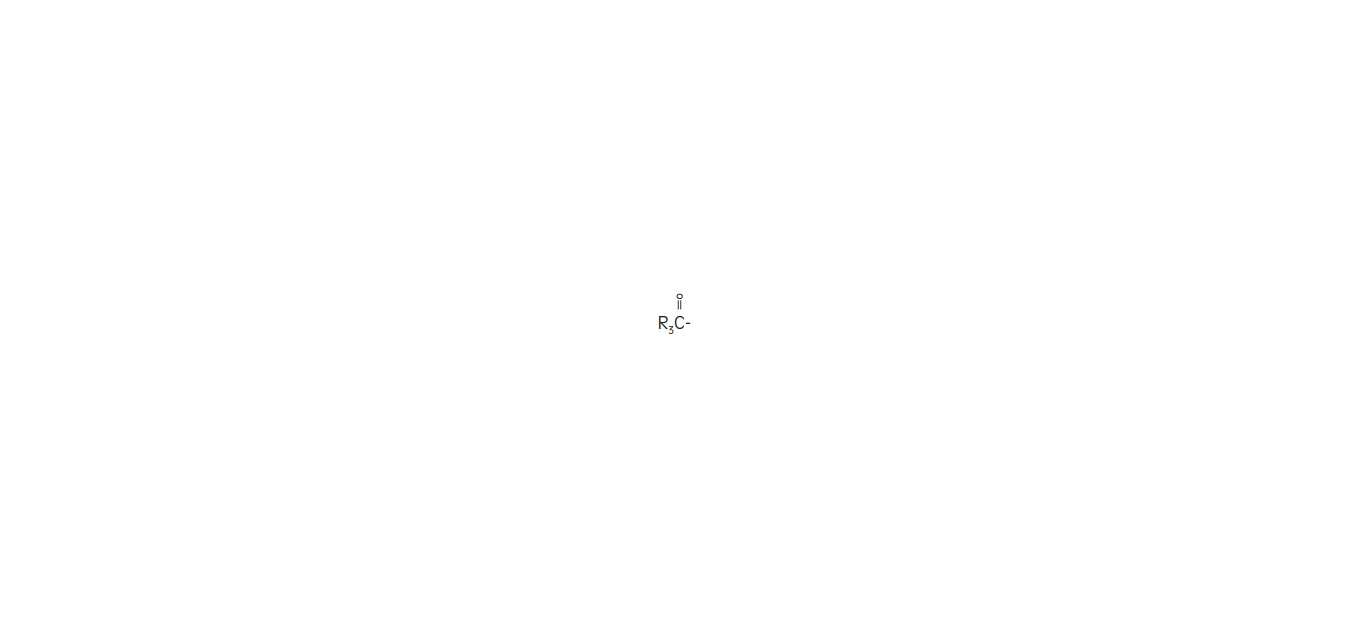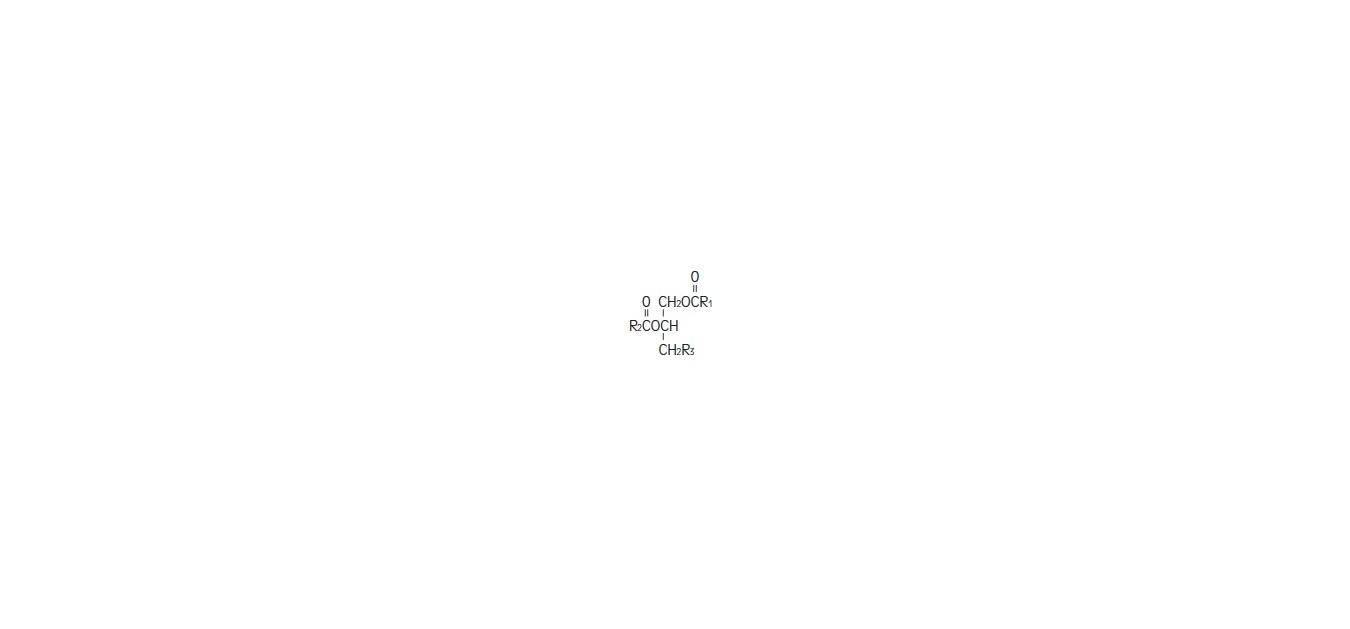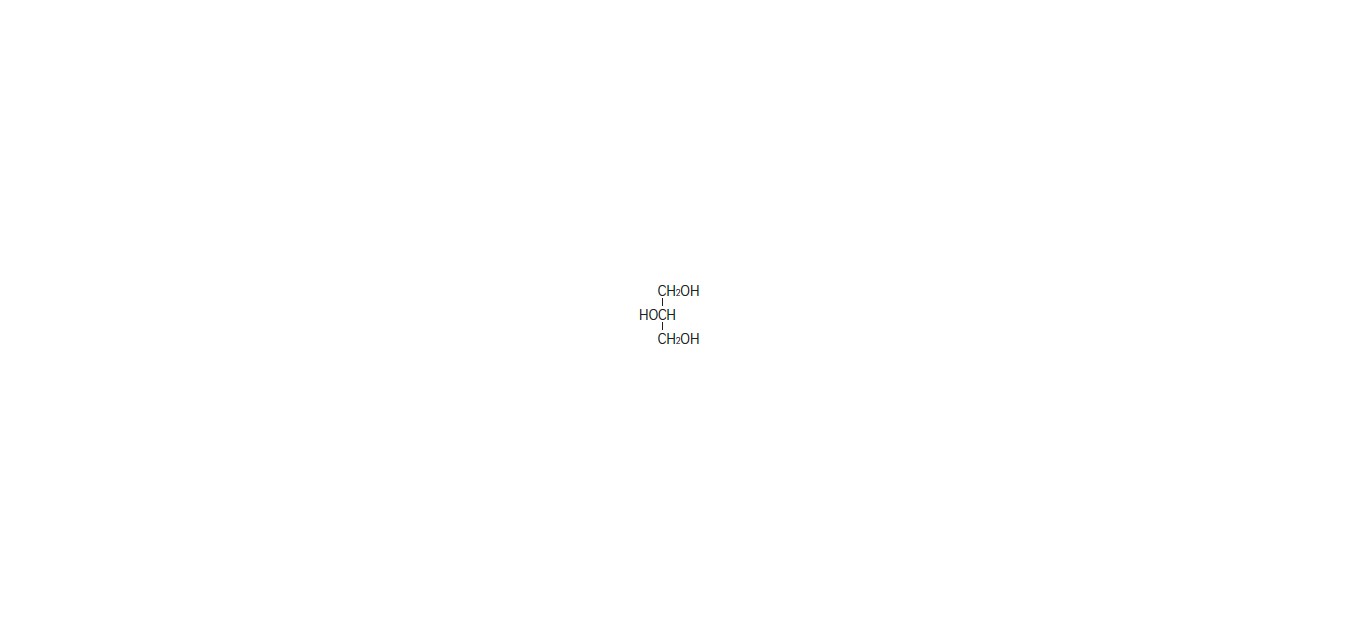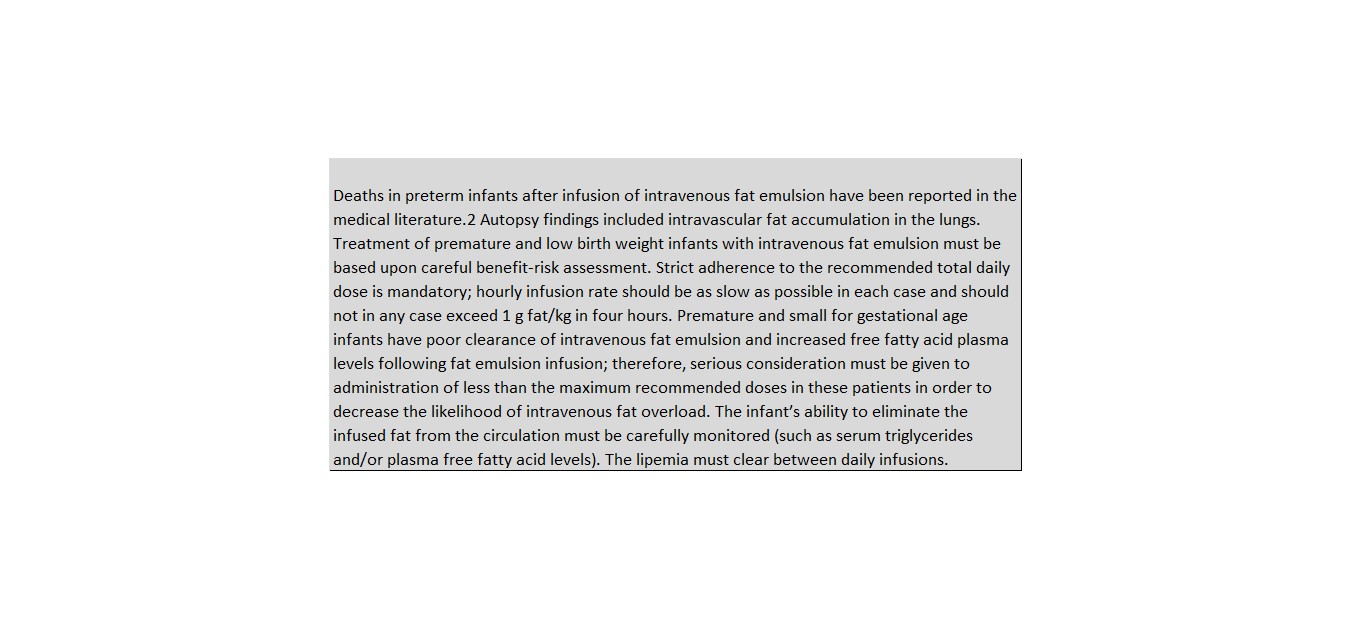 DRUG LABEL: INTRALIPID
NDC: 51662-1333 | Form: EMULSION
Manufacturer: HF Acquisition Co LLC, DBA HealthFirst
Category: prescription | Type: HUMAN PRESCRIPTION DRUG LABEL
Date: 20200222

ACTIVE INGREDIENTS: SOYBEAN OIL 20 g/100 mL
INACTIVE INGREDIENTS: EGG PHOSPHOLIPIDS; GLYCERIN; SODIUM HYDROXIDE

INTRALIPID 20% 250mL BAG

SPL UNCLASSIFIED

A 20% I.V. Fat Emulsion

DESCRIPTION

Intralipid® 20% (A 20% Intravenous Fat Emulsion) is a sterile, non-pyrogenic fat emulsion prepared for intravenous administration as a source of calories and essential fatty acids. It is made up of 20% Soybean Oil, 1.2% Egg Yolk Phospholipids, 2.25% Glycerin, and Water for Injection. In addition, sodium hydroxide has been added to adjust the pH so that the final product pH is 8. pH range is 6 to 8.9.

The soybean oil is a refined natural product consisting of a mixture of neutral triglycerides of predominantly unsaturated fatty acids with the following structure:

where

,

,

and

are saturated and unsaturated fatty acid residues.

The major component fatty acids are linoleic acid (44-62%), oleic acid (19-30%), palmitic acid (7-14%), α-linolenic acid (4-11%) and stearic acid (1.4-5.5%).1 These fatty acids have the following chemical and structural formulas:

Purified egg phosphatides are a mixture of naturally occurring phospholipids which are isolated from the egg yolk. These phospholipids have the following general structure:

and

contain saturated and unsaturated fatty acids that abound in neutral fats. R3 is primarily either the choline or ethanolamine ester of phosphoric acid.

Glycerin is chemically designated C3H8O3 and is a clear colorless, hygroscopic syrupy liquid. It has the following structural formula:

Intralipid® 20% (A 20% Intravenous Fat Emulsion) has an osmolality of approximately 350 mOsmol/kg water (which represents 260 mOsmol/L of emulsion) and contains emulsified fat particles of approximately 0.5 micron size.

The total caloric value, including fat, phospholipid and glycerin, is 2.0 kcal per mL of Intralipid® 20%. The phospholipids present contribute 47 milligrams or approximately 1.5 mmol of phosphorus per 100 mL of the emulsion.

The primary plastic container (Biofine™), is made from multilayered film specifically designed for parenteral nutrition drug products. The film is polypropylene based comprising three co-extruded layers. It contains no plasticizers and exhibits virtually no leachables. The container does not contain DEHP (di(2-ethylhexyl)phthalate) or PVC. The container is nontoxic and biologically inert. This product is not made with natural rubber latex.

The container-emulsion unit is a closed system and is not dependent upon entry of external air during administration.

The container is overwrapped to provide protection from the physical environment and to provide an additional moisture barrier when necessary.

CLINICAL PHARMACOLOGY

Intralipid® 20% is metabolized and utilized as a source of energy causing an increase in heat production, decrease in respiratory quotient and increase in oxygen consumption. The infused fat particles are cleared from the blood stream in a manner thought to be comparable to the clearing of chylomicrons.

Intralipid® 20% will prevent the biochemical lesions of essential fatty acid deficiency (EFAD), and correct the clinical manifestations of the EFAD syndrome.

INDICATIONS & USAGE

Intralipid® 20% is indicated as a source of calories and essential fatty acids for patients requiring parenteral nutrition for extended periods of time (usually for more than 5 days) and as a source of essential fatty acids for prevention of EFAD.

CONTRAINDICATIONS

The administration of Intralipid® 20% is contraindicated in patients with disturbances of normal fat metabolism such as pathologic hyperlipemia, lipoid nephrosis or acute pancreatitis if accompanied by hyperlipidemia.

WARNINGS

Caution should be exercised in administering of Intralipid® 20% (A 20% Intravenous Fat Emulsion) to patients with severe liver damage, pulmonary disease, anemia or blood coagulation disorders, or when there is danger of fat embolism.

WARNING: This product contains aluminum that may be toxic. Aluminum may reach toxic levels with prolonged parenteral administration if kidney function is impaired. Premature neonates are particularly at risk because their kidneys are immature, and they require large amounts of calcium and phosphate solutions, which contain aluminum.

Research indicates that patients with impaired kidney function, including premature neonates, who receive parenteral levels of aluminum at greater than 4 to 5 mcg/kg/day accumulate aluminum at levels associated with central nervous system and bone toxicity. Tissue loading may occur at even lower rates of administration.

PRECAUTIONS

When Intralipid® 20% is administered, the patients capacity to eliminate the infused fat from the circulation must be monitored by use of an appropriate laboratory determination of serum triglycerides. Overdosage must be avoided.

During long term intravenous nutrition with Intralipid® 20%, liver function tests should be performed. If these tests indicate that liver function is impaired, the therapy should be withdrawn.

Frequent (some advise daily) platelet counts should be done in neonatal patients receiving parenteral nutrition with Intralipid® 20%.

Drug product contains no more than 25 mcg/L of aluminum.

Carcinogenesis, Mutagenesis, Impairment of Fertility:

Studies with Intralipid® have not been performed to evaluate carcinogenic potential, mutagenic potential, or effects on fertility.

Pregnancy Category C: Animal reproduction studies have not been conducted with Intralipid®. It is also not known whether Intralipid® can cause fetal harm when administered to a pregnant woman or can affect reproduction capacity. Intralipid® should be given to a pregnant woman only if clearly needed.

Nursing Mothers: Caution should be exercised when Intralipid® is administered to a nursing woman.

Pediatric Use: See DOSAGE & ADMINISTRATION.

AVOID OVERDOSAGE ABSOLUTELY.

ADVERSE REACTIONS

The adverse reactions observed can be separated into two classes:

Those more frequently encountered are due: either to contamination of the intravenous catheter and result in sepsis, or to vein irritation by concurrently infused hypertonic solutions and may result in thrombophlebitis. These adverse reactions are inseparable from the hyperalimentation procedure with or without Intralipid® 20% (A 20% I.V. Fat Emulsion).
Less frequent reactions more directly related to Intralipid® 20% are: a) immediate or early adverse reactions, each of which has been reported to occur in clinical trials, in an incidence of less than 1%; dyspnea, cyanosis, allergic reactions, hyperlipemia, hypercoagulability, nausea, vomiting, headache, flushing, increase in temperature, sweating, sleepiness, pain in the chest and back, slight pressure over the eyes, dizziness, and irritation at the site of infusion, and, rarely, thrombocytopenia in neonates; b) delayed adverse reactions such as hepatomegaly, jaundice due to central lobular cholestasis, splenomegaly, thrombocytopenia, leukopenia, transient increases in liver function tests, and overloading syndrome (focal seizures, fever, leukocytosis, hepatomegaly, splenomegaly and shock).

The deposition of a brown pigmentation in the reticuloendothelial system, the so-called “intravenous fat pigment,” has been reported in patients infused with Intralipid® 20%. The causes and significance of this phenomenon are unknown.

OVERDOSAGE

In the event of fat overload during therapy, stop the infusion of Intralipid® 20% until visual inspection of the plasma, determination of triglyceride concentrations, or measurement of plasma light-scattering activity by nephelometry indicates the lipid has cleared. Re-evaluate the patient and institute appropriate corrective measures. See WARNINGS and PRECAUTIONS.

DOSAGE & ADMINISTRATION

Intralipid® 20% should be administered as a part of Intravenous nutrition via peripheral vein or by central venous infusion.

Adult Patients

The initial rate of infusion in adults should be 0.5 mL/minute for the first 15 to 30 minutes of infusion. If no untoward reactions occur (see ADVERSE REACTIONS section), the infusion rate can be increased to 1 mL/minute. Not more than 500 mL of Intralipid® 20% should be infused into adults on the first day of therapy. If the patient has no untoward reactions, the dose can be increased on the following day. The daily dosage should not exceed 2.5 g of fat/kg of body weight (12.5 mL of Intralipid® 20% per kg). Intralipid® 20% (A 20% I.V. Fat Emulsion) should make up no more than 60% of the total caloric input to the patient. Carbohydrate and a source of amino acids should comprise the remaining caloric input.

Pediatric Patients

The dosage for premature infants starts at 0.5 g fat/kg body weight/24 hours (2.5 mL Intralipid® 20%) and may be increased in relation to the infant’s ability to eliminate fat. The maximum dosage recommended by the American Academy of Pediatrics is 3 g fat/kg/24 hours.3

The initial rate of infusion in older pediatric patients should be no more than 0.05 mL/minute for the first 10 to 15 minutes. If no untoward reactions occur, the rate can be changed to permit infusion of 0.5 mL of Intralipid® 20%/kg/hour. The daily dosage should not exceed 3 g of fat/kg of body weight.3 Intralipid® 20% should make up no more than 60% of the total caloric input to the patient. Carbohydrate and a source of amino acids should comprise the remaining caloric input.

Essential Fatty Acid Deficiency

When Intralipid® 20% is administered to correct essential fatty acid deficiency, eight to ten percent of the caloric input should be supplied by Intralipid® 20% in order to provide adequate amounts of linoleic and linolenic acids. When EFAD occurs together with stress, the amount of Intralipid® 20% needed to correct the deficiency may be increased.

Administration

See MIXING GUIDELINES AND LIMITATIONS section for information regarding mixing this fat emulsion with other parenteral fluids.

Intralipid® 20% can be infused into the same central or peripheral vein as carbohydrate/amino acids solutions by means of a Y-connector near the infusion site. This allows for mixing of the emulsion immediately before entering the vein or for alternation of each parenteral fluid. If infusion pumps are used, flow rates of each parenteral fluid should be controlled with a separate pump. Fat emulsion may also be infused through a separate peripheral site. Use a 1.2 micron filter with Intralipid® 20%. Filters of less than 1.2 micron pore size must not be used. Conventional administration sets and TPN pooling bags contain polyvinyl chloride (PVC) components that have DEHP (di(2-ethylhexyl) phthalate) as a plasticizer. Fat‑containing fluids such as Intralipid® 20% extract DEHP from these PVC components and it may be advisable to consider infusion of Intralipid® 20% through a non-DEHP administration set.

Do not use any bag in which there appears to be an oiling out on the surface of the emulsion.

Parenteral drug products should be inspected visually for particulate matter and discoloration prior to administration whenever solution and container permit.

MIXING GUIDELINES AND LIMITATIONS

Intralipid® 20% (A 20% I.V. Fat Emulsion) may be mixed with Amino Acid and Dextrose Injections where compatibility have been demonstrated. Additives known to be incompatible should not be used. Please consult with pharmacist. If, in the informed judgment of the physician, it is deemed advisable to introduce additives, use aseptic technique. Mix thoroughly when additives have been introduced. Do not store solutions containing additives (e.g., Vitamins and Minerals).

When being mixed the following proper mixing sequence must be followed to minimize pH related problems by ensuring that typically acidic Dextrose Injections are not mixed with lipid emulsions alone:

1. Transfer Dextrose Injection to the TPN Admixture Container

2. Transfer Amino Acid Injection

3. Transfer Intralipid® 20% (A 20% Intravenous Fat Emulsion)

Note: Amino Acid Injection, Dextrose Injection and Intralipid® 20% may be simultaneously transferred to the admixture container. Admixing should be accompanied by gentle agitation to avoid localized concentration effects.

Additives must not be added directly to Intralipid® 20% and in no case should Intralipid® 20% be added to the TPN container first. Bags should be shaken gently after each addition to minimize localized concentration.

If the admixture is not used immediately, the in-use storage time and conditions prior to use are the responsibility of the user and should normally not be longer than 24 hours at 2-8°C.

After removal from storage at 2-8°C, the admixture should be infused within 24 hours.

It is essential that the admixture be prepared using strict aseptic techniques as this nutrient mixture is a good growth medium for microorganisms.

Supplemental electrolytes, trace metals or multivitamins may be required in accordance with the prescription of the attending physician.

The prime destabilizers of emulsions are excessive acidity (low pH) and inappropriate electrolyte content. Careful consideration should be given to additions of divalent cations (Ca++ and Mg++) which have been shown to cause emulsion instability. Amino acid solutions exert a buffering effect protecting the emulsion. The admixture should be inspected carefully for “breaking or oiling out“ of the emulsion. “Breaking or oiling out” is described as the separation of the emulsion and can be visibly identified by a yellowish streaking or the accumulation of yellowish droplets in the admixed emulsion. The admixture should also be examined for particulates. The admixture must be discarded if any of the above is observed.

HOW SUPPLIED

INTRALIPID 20% is supplied in the following dosage forms.
NDC 51662-1333-1
INTRALIPID 20% 250mL BAG

HF Acquisition Co LLC, DBA HealthFirst
Mukilteo, WA 98275

Also supplied in the following manufacture supplied dosage forms

Intralipid® 20% is supplied as a sterile emulsion in the following fill sizes: 100 mL, 250 mL and 500 mL.
100 mL: 0338-0519-58
250 mL: 0338-0519-09
500 mL: 0338 0519-13

Intralipid® 20% is also available as Pharmacy Bulk Package in the following fill size.

1000 mL: 0338-0519-14

STORAGE

Intralipid® 20% should not be stored above 25°C (77°F). Do not freeze Intralipid® 20%. If accidentally frozen, discard the bag.

REFERENCES

Padley FB: “Major Vegetable Fats,” The Lipid Handbook (Gunstone FD, Harwood JL, Padley FB, eds.), Chapman and Hall Ltd., Cambridge, UK (1986), pp. 88-9.
Levene MI, Wigglesworth JS, Desai R: Pulmonary fat accumulation after Intralipid® infusion in the preterm infant. Lancet 1980; 2(8199):815-8.
American Academy of Pediatrics: Use of intravenous fat emulsion in pediatric patients. Pediatrics 1981; 68:5(Nov) 738-43.

SPL UNCLASSIFIED

(Rev September 2016)

Manufactured for
Baxter Healthcare Corporation
Deerfield, IL 60015 USA

Manufactured by
Fresenius Kabi,
Uppsala, Sweden

Intralipid® is a registered trademark of Fresenius Kabi AB.

INSTRUCTIONS FOR USE

Instruction for Use - Intralipid® 20% Container

then,

then,

then,

then,

then,